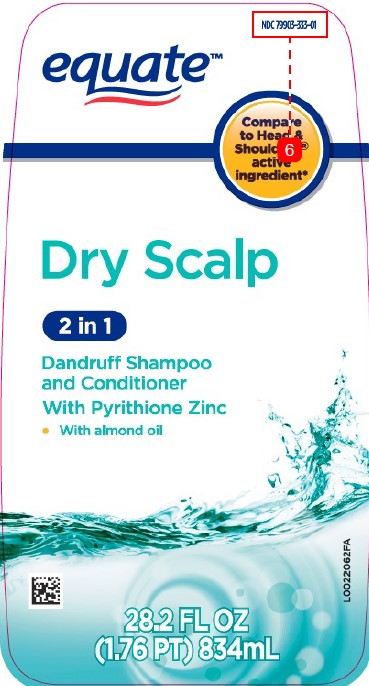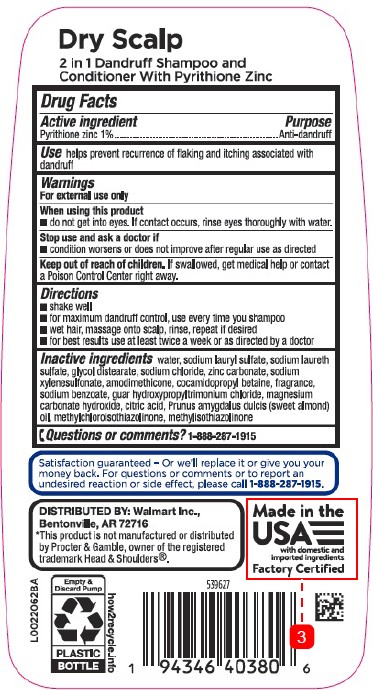 DRUG LABEL: Dry Scalp
NDC: 79903-333 | Form: SHAMPOO
Manufacturer: Walmart Inc.
Category: otc | Type: HUMAN OTC DRUG LABEL
Date: 20260227

ACTIVE INGREDIENTS: PYRITHIONE ZINC 10 mg/1 mL
INACTIVE INGREDIENTS: WATER; SODIUM LAURYL SULFATE; SODIUM LAURETH SULFATE; GLYCOL DISTEARATE; SODIUM CHLORIDE; ZINC CARBONATE; SODIUM XYLENESULFONATE; AMODIMETHICONE (800 CST); COCAMIDOPROPYL BETAINE; SODIUM BENZOATE; GUAR HYDROXYPROPYLTRIMONIUM CHLORIDE (1.7 SUBSTITUENTS PER SACCHARIDE); MAGNESIUM CARBONATE HYDROXIDE; CITRIC ACID MONOHYDRATE; ALMOND OIL; METHYLCHLOROISOTHIAZOLINONE; METHYLISOTHIAZOLINONE

Equate 296.007/296AT-AW
Dandruff Shampoo, Dry Scalp 2 in 1

Claims

Dry Scalp

2 in 1 Dandruff Shampoo and Conditioner With Pyrithione Zinc

Active ingredient

Pyrithione zinc 1%

Purpose

Anti-Dandruff

Use

helps prevent recurrence of flaking and itching associated with dandruff

Warnings

For external use only

When using this product

- do not get into eyes. If contact occurs, rinse eyes thoroughly with water.

Stop use and ask a doctor if

- condition worsens or does not improve after reqular use as directed

Keep out of reach of children.

If swallowed, get medical help or contact a Poison Control Center right away.

Directions

- shake well
- for maximum dandruff control, use every time you shampoo
- wet hair, massage onto scalp, rinse, repeat if desired
- for best results at least twice a week or as directed by a doctor

Inactive ingredients

water, sodium lauryl sulfate, sodium laureth sulfate, glycol distearate, sodium chloride, zinc carbonate, sodium xlenesulfonate, amodimethicone, cocamidopropyl betaine, fragrance, sodium benzoate, guar hydroxypropyltrimonium chloride, magnesium carbonate hydroxide, citric acid, prunus amygdalus dulcis (sweet almond) oil, methylchloroisothiazolinone, methylisothiazolinone

Questions or comments?

1-888-287-1915

ADVERSE REACTION

Satisfaction guaranteed - Or we'll replace it or give you your money back. For questions or comments or to report an undesired reaction or side effect, please call 1-888-287-1915.

DISTRIBUTED BY: Walmart Inc.,

Bentonville, AR 72716

*This product is not manufactured or distributed by Procter & Gamble, owner of the registered trademark Head & Shoulders®.

Made in the USA with domestic and imported ingredients

Factory Certified

Empty & Discard Pump

PLASTIC BOTTLE

how2recycle.info

PRINCIPAL DISPLAY PANEL

NDC 79903-333-01

equate™

Compare to Head & Shoulders® active ingredient*

Dry Scalp

2 in 1

Dandruff Shampoo and Conditioner

With Pyrithione Zinc

- With almond oil

28.2 FL OZ (1.76 PT) 834 mL